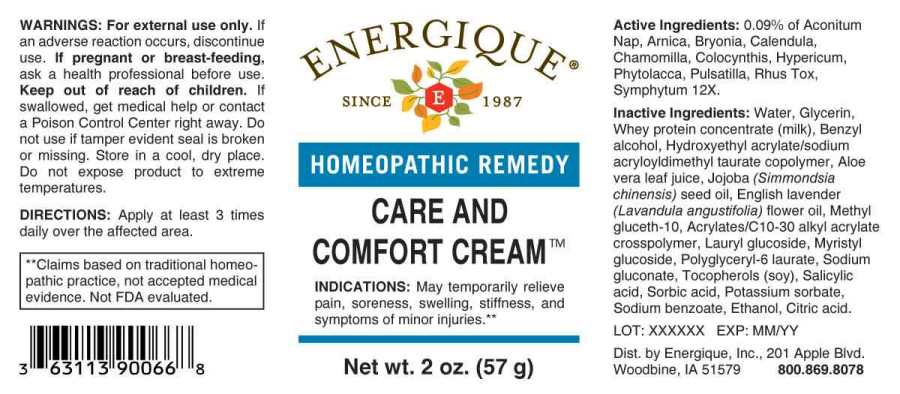 DRUG LABEL: Care and Comfort Cream
NDC: 44911-0639 | Form: CREAM
Manufacturer: Energique, Inc.
Category: homeopathic | Type: HUMAN OTC DRUG LABEL
Date: 20241024

ACTIVE INGREDIENTS: ACONITUM NAPELLUS WHOLE 12 [hp_X]/1 g; ARNICA MONTANA WHOLE 12 [hp_X]/1 g; BRYONIA ALBA ROOT 12 [hp_X]/1 g; CALENDULA OFFICINALIS FLOWERING TOP 12 [hp_X]/1 g; MATRICARIA CHAMOMILLA WHOLE 12 [hp_X]/1 g; CITRULLUS COLOCYNTHIS FRUIT PULP 12 [hp_X]/1 g; HYPERICUM PERFORATUM WHOLE 12 [hp_X]/1 g; PHYTOLACCA AMERICANA ROOT 12 [hp_X]/1 g; PULSATILLA PRATENSIS WHOLE 12 [hp_X]/1 g; TOXICODENDRON PUBESCENS LEAF 12 [hp_X]/1 g; COMFREY ROOT 12 [hp_X]/1 g
INACTIVE INGREDIENTS: WATER; GLYCERIN; WHEY; HYDROXYETHYL ACRYLATE/SODIUM ACRYLOYLDIMETHYL TAURATE COPOLYMER (100000 MPA.S AT 1.5%); BENZYL ALCOHOL; SALICYLIC ACID; SORBIC ACID; METHYL GLUCETH-10; LAURYL GLUCOSIDE; MYRISTYL GLUCOSIDE; POLYGLYCERYL-10 LAURATE; CARBOMER INTERPOLYMER TYPE A (ALLYL SUCROSE CROSSLINKED); ALOE VERA LEAF; JOJOBA OIL; LAVENDER OIL; SODIUM GLUCONATE; .ALPHA.-TOCOPHEROL; POTASSIUM SORBATE; SODIUM BENZOATE; CITRIC ACID MONOHYDRATE; ALCOHOL

DRUG FACTS:

ACTIVE INGREDIENTS

0.09% of Aconitum Napellus 12X, Arnica Montana 12X, Bryonia (Alba) 12X, Calendula Officinalis 12X, Chamomilla 12X, Colocynthis 12X, Hypericum Perforatum 12X, Pulsatilla (Pratensis) 12X, Rhus Tox 12X, Symphytum Officinale 12X.

INDICATIONS:

May temporarily relieve pain, soreness, swelling, stiffness, and symptoms of minor injuries.**

**Claims based on traditional homeopathic practice, not accepted medical evidence. Not FDA evaluated.

WARNINGS:

For external use only. If an adverse reaction occurs, discontinue use.

If pregnant or breast-feeding, ask a health professional before use.

Keep out of reach of children. If swallowed, get medical help or contact a Poison Control Center right away.

Do not use if tamper evident seal is broken or missing. Store in a cool, dry place.

Do not expose product to extreme temperatures.

Keep out of reach of children. If swallowed, get medical help or contact a Poison Control Center right away.

DIRECTIONS:

Apply at least 3 times daily over the affected area.

INDICATIONS:

May temporarily relieve pain, soreness, swelling, stiffness, and symptoms of minor injuries.**

**Claims based on traditional homeopathic practice, not accepted medical evidence. Not FDA evaluated.

INACTIVE INGREDIENTS:

Water, Glycerin, Whey protein concentrate (milk), Benzyl alcohol, Hydroxyethyl Acrylate/Sodium Acryloyldimethyl Taurate Copolymer, Aloe Vera leaf juice, Jojoba (Simmondsia Chinensis) Seed Oil, English Lavender (Lavandula Angustifolia) flower oil, Methyl Gluceth-10, Acrylates/C10-30 Alkyl Acrylate Crosspolymer, Lauryl Glucoside, Myristyl Glucoside, Polyglyceryl-6 Laurate, Sodium Gluconate, Tocopherols (soy), Salicylic Acid, Sorbic Acid, Potassium Sorbate, Sodium Benzoate, Ethanol, Citric Acid.

QUESTIONS:

Dist. by Energique, Inc.

201 Apple Blvd

Woodbine, IA 51579 800-869-8078

PACKAGE LABEL DISPLAY:

ENERGIQUE

SINCE 1987

HOMEOPATHIC REMEDY

CARE AND

COMFORT CREAM

Net wt. 2 oz. (57 g)